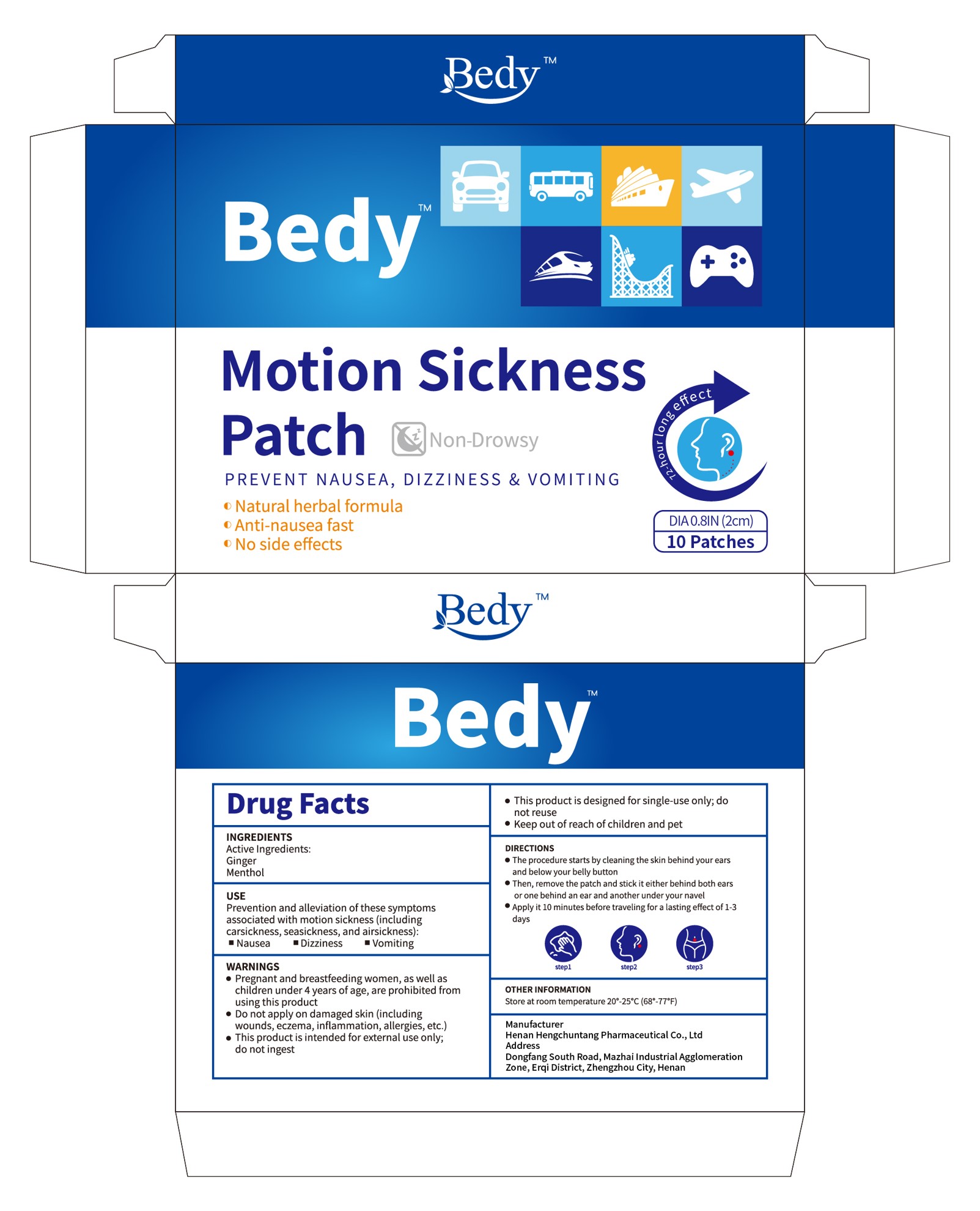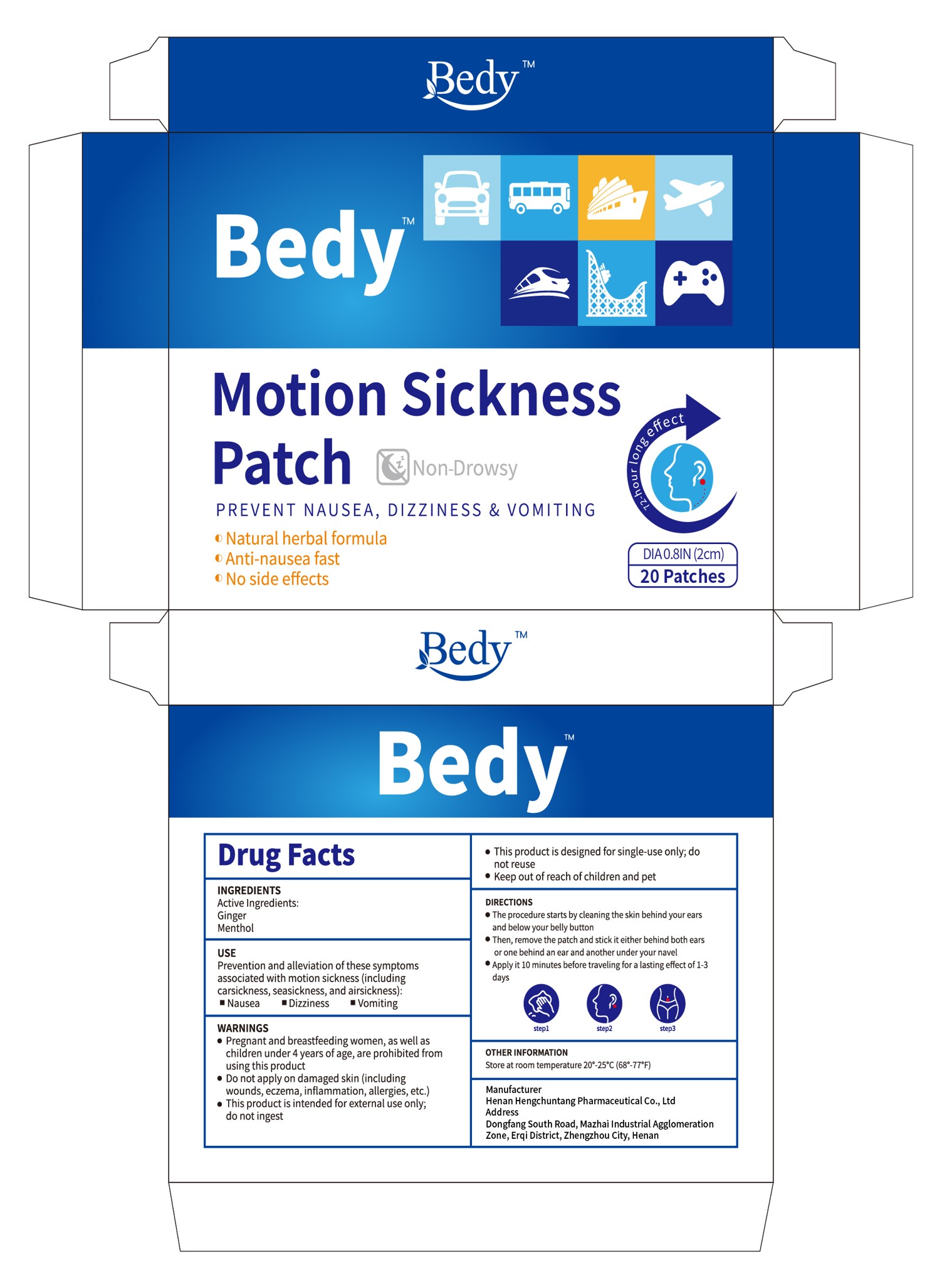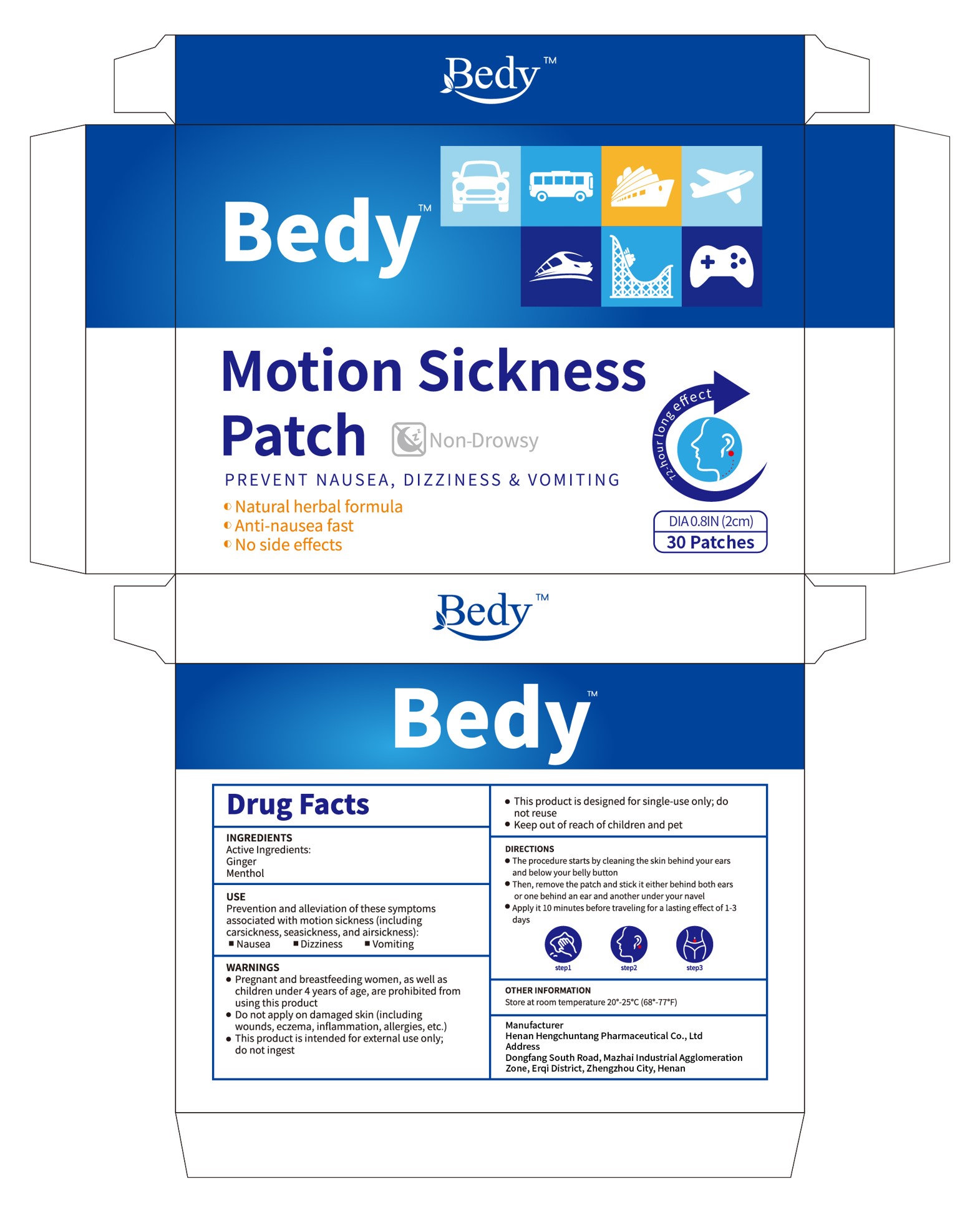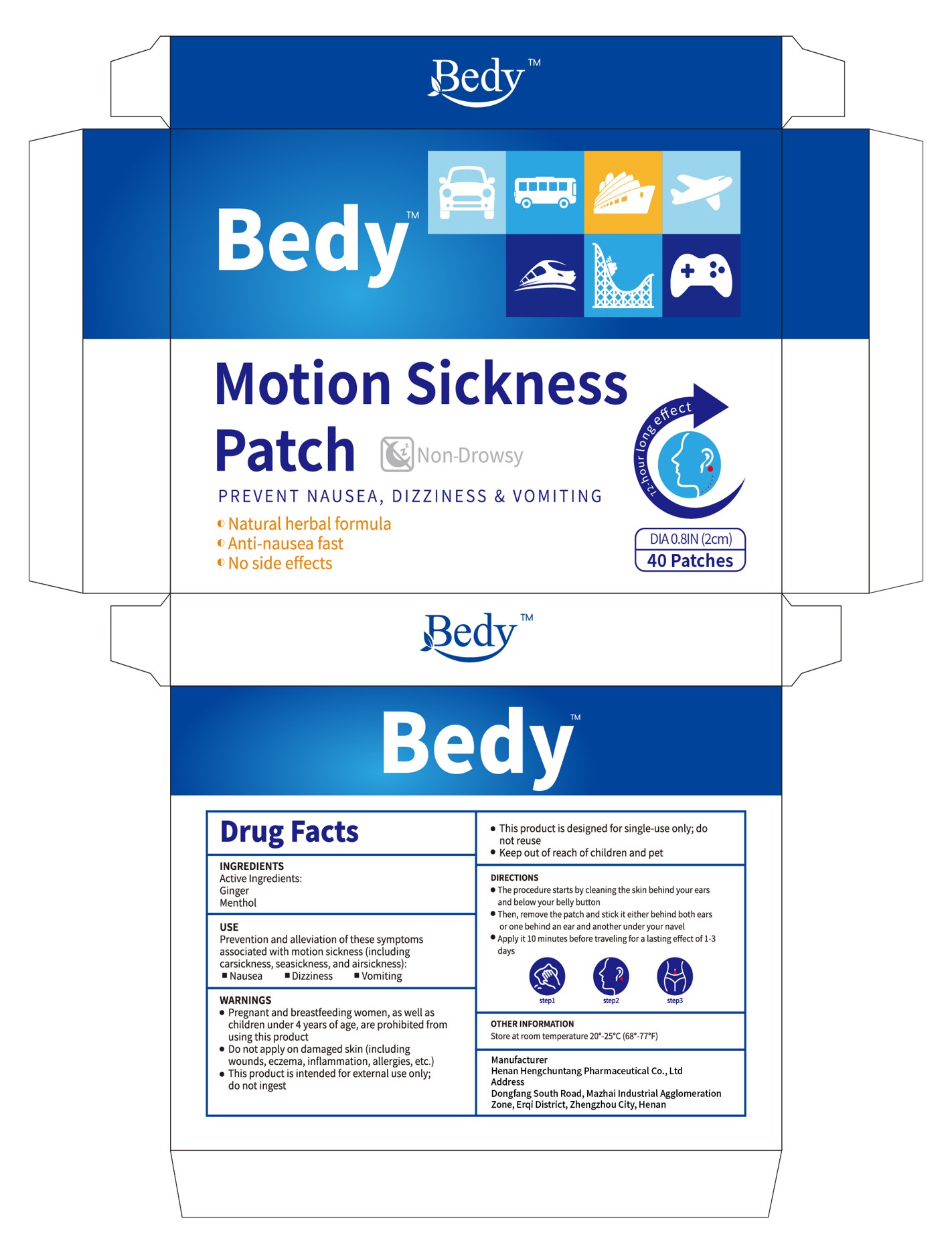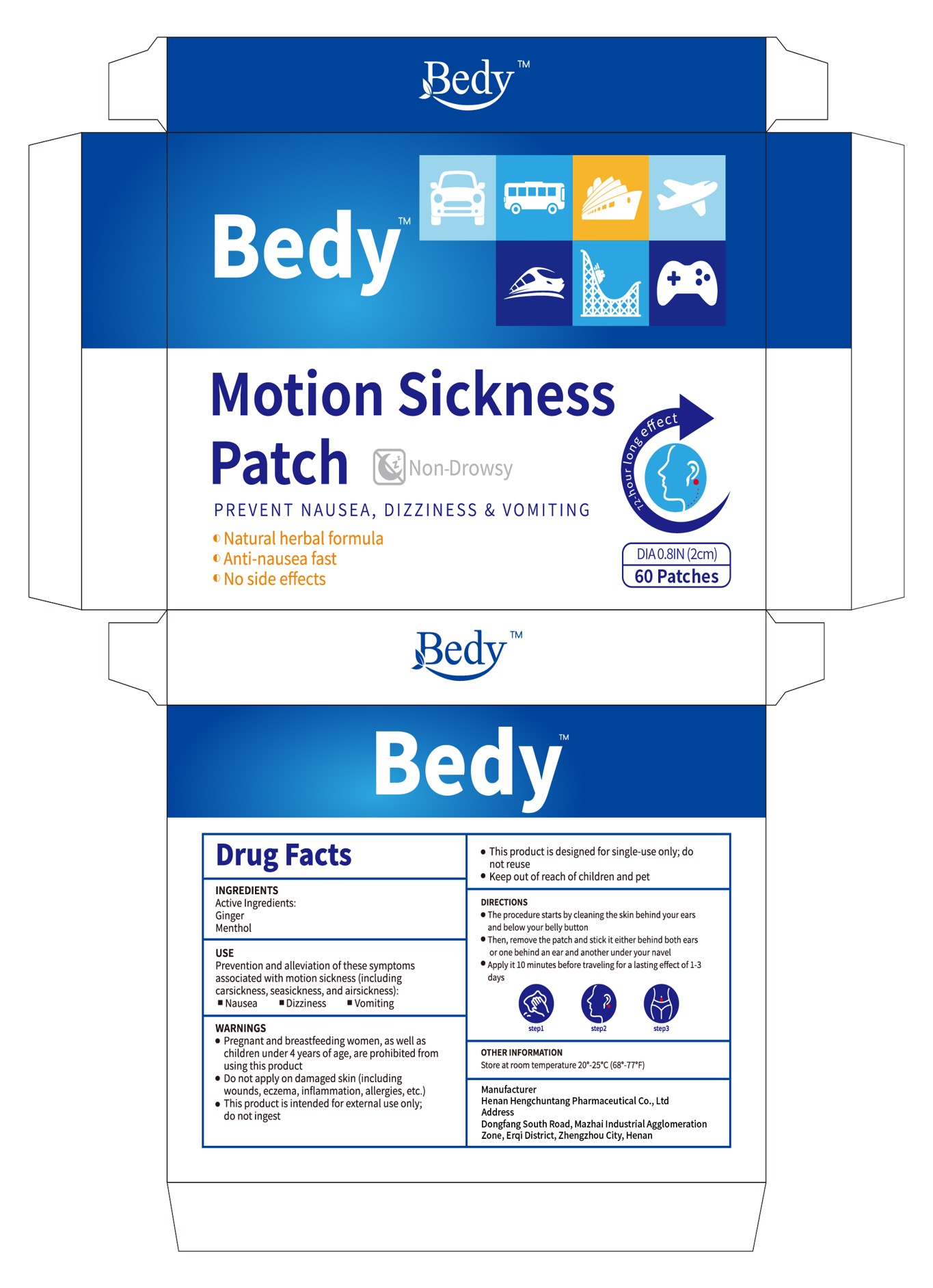 DRUG LABEL: Bedy Motion Sickness Patches
NDC: 85152-003 | Form: PATCH
Manufacturer: Henan Hengchuntang Pharmaceutical Co., Ltd
Category: otc | Type: HUMAN OTC DRUG LABEL
Date: 20250217

ACTIVE INGREDIENTS: MENTHOL 2 g/100 g; GINGER 1 g/100 g
INACTIVE INGREDIENTS: ETHYLENE-VINYL ACETATE COPOLYMER (28% VINYL ACETATE); COTTON

Active Ingredient

Ginger
Menthol

Inactive ingredient

EVA-28

COTTON

Purpose

PREVENT NAUSEA,DIZZINESS &VOMITINGo

Natural herbal formula
Anti-nausea fast
No side effects

When using

Then, remove the patch and stick it either behind both earsor one behind an ear and another under your navel

Do not use

Pregnant women, breastfeeding mothers, children under the age of4 should not use.Donot use if the skin has abnormalities, wounds, eczema, inflammation, allergies.Pleasekeep it out of reach of children and pets.

keep it out of reach of children

Please keep it out of reach of children and pets.
For external use only.

Doseage

Apply it 10 minutes before traveling for a lasting effect of 1-3days

Warning

Pregnant women, breastfeeding mothers,children under the age of 4 should not use.Do not use if the skin has abnormalities, wounds, eczema, inflammation, allergies.Please keep it out of reach of children and pets.For external use only.

Indication

1.Tear open the package, take out the patch, peel off the white anti-adhesive layer, andstick the patchbehind the ear or the navel (please dry the sweat from the ear and thenavel).2.Use it 10 minutes before boarding a car, airplane or boat